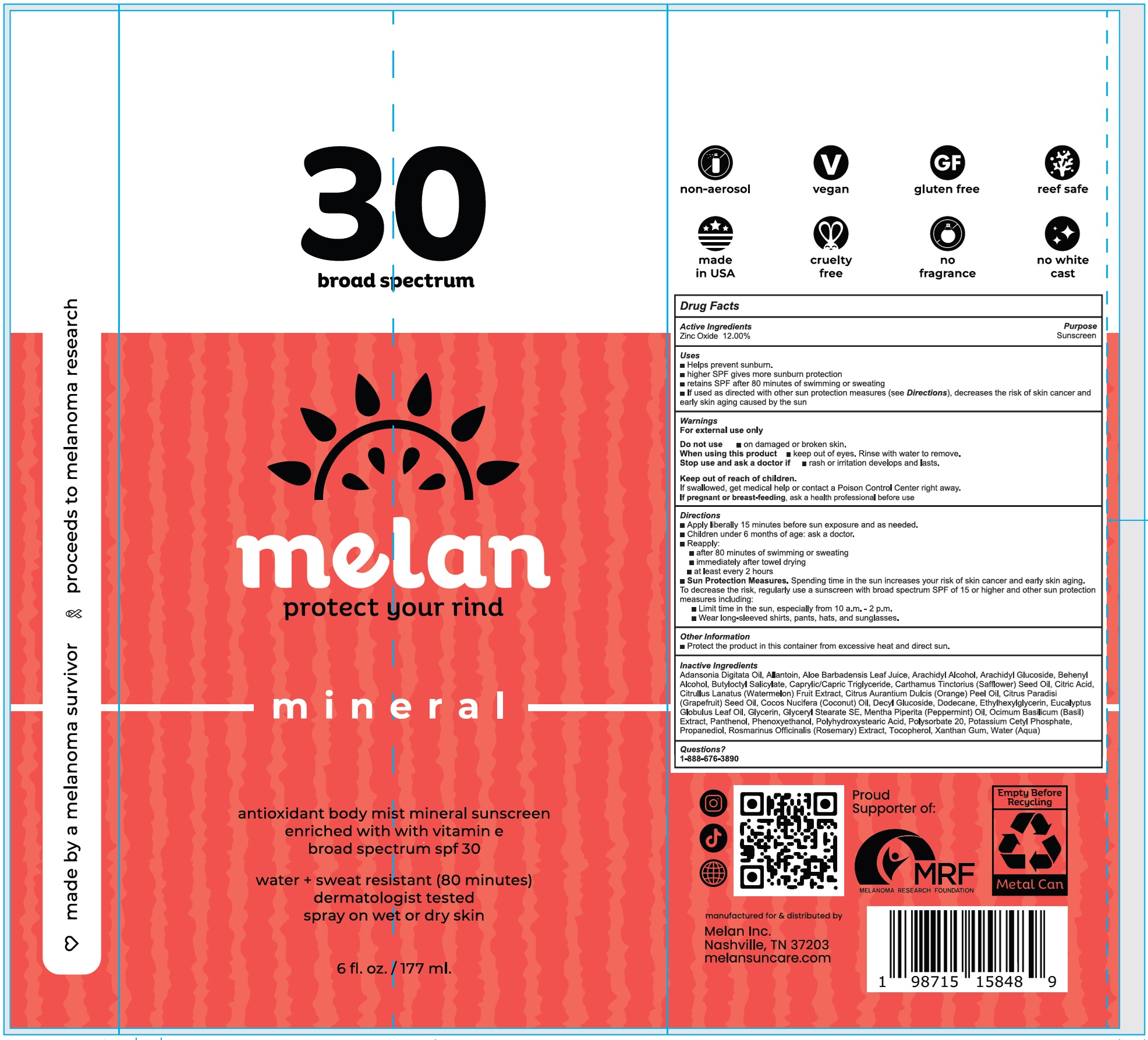 DRUG LABEL: Melan Mineral Antioxidant Body Mist Mineral Sunscreen SPF 30
NDC: 84294-601 | Form: LIQUID
Manufacturer: MELAN INC.
Category: otc | Type: HUMAN OTC DRUG LABEL
Date: 20241114

ACTIVE INGREDIENTS: ZINC OXIDE 120 mg/1 mL
INACTIVE INGREDIENTS: ADANSONIA DIGITATA SEED OIL; ALLANTOIN; ALOE VERA LEAF; ARACHIDYL ALCOHOL; ARACHIDYL GLUCOSIDE; BEHENYL ALCOHOL; BUTYLOCTYL SALICYLATE; CAPRYLIC/CAPRIC TRIGLYCERIDE; CARTHAMUS TINCTORIUS (SAFFLOWER) SEED OIL; CITRIC ACID MONOHYDRATE; CITRULLUS LANATUS (WATERMELON) FRUIT EXTRACT; CITRUS AURANTIUM DULCIS (ORANGE) PEEL OIL; CITRUS PARADISI (GRAPEFRUIT) SEED OIL; COCOS NUCIFERA (COCONUT) OIL; DECYL GLUCOSIDE; DODECANE; ETHYLHEXYLGLYCERIN; EUCALYPTUS GLOBULUS LEAF OIL; GLYCERIN; GLYCERYL STEARATE SE; MENTHA PIPERITA (PEPPERMINT) OIL; BASIL; PANTHENOL; PHENOXYETHANOL; POLYSORBATE 20; POTASSIUM CETYL PHOSPHATE; PROPANEDIOL; ROSMARINUS OFFICINALIS (ROSEMARY) EXTRACT; TOCOPHEROL; XANTHAN GUM; WATER

Melan Mineral Antioxidant Body Mist Mineral Sunscreen SPF 30

Active Ingredients

Zinc Oxide 12.00%

Purpose

Sunscreen

Uses

- Helps prevent sunburn.
- higher SPF gives more sunburn protection
- retains SPF after 80 minutes of swimming or sweating
- If used as directed with other sun protection measures (see Directions), decreases the risk of skin cancer and early skin aging caused by the sun

Warnings

For external use only

Do not use

- on damaged or broken skin.

When using this product

- keep out of eyes. Rinse with water to remove.

Stop use and ask a doctor if

- rash or irritation develops and lasts.

Keep out of reach of children.

If swallowed, get medical help or contact a Poison Control Center right away.

If pregnant or breast-feeding,

ask a health professional before use

Directions

- Apply liberally 15 minutes before sun exposure and as needed.
- Children under 6 months of age: ask a doctor.
- Reapply:
- after 80 minutes of swimming or sweating
- immediately after towel drying
- at least every 2 hours
- Sun Protection Measures.Spending time in the sun increases your risk of skin cancer and early skin aging. To decrease the risk, regularly use a sunscreen with broad spectrum SPF of 15 or higher and other sun protection measures including:
- Limit time in the sun, especially from 10 a.m. - 2 p.m.
- Wear long-sleeved shirts, pants, hats, and sunglasses.

Other Information

- Protect the product in this container from excessive heat and direct sun.

Inactive Ingredients

Adansonia Digitata Oil, Allantoin, Aloe Barbadensis Leaf Juice, Arachidyl Alcohol, Arachidyl Glucoside, Behenyl Alcohol, Butyloctyl Salicylate, Caprylic/Capric Triglyceride, Carthamus Tinctorius (Safflower) Seed Oil, Citric Acid, Citrullus Lanatus (Watermelon) Fruit Extract, Citrus Aurantium Dulcis (Orange) Peel Oil, Citrus Paradisi (Grapefruit) Seed Oil, Cocos Nucifera (Coconut) Oil, Decyl Glucoside, Dodecane, Ethylhexylglycerin, Eucalyptus Globulus Leaf Oil, Glycerin, Glyceryl Stearate SE, Mentha Piperita (Peppermint) Oil, Ocimum Basilicum (Basil) Extract, Panthenol, Phenoxyethanol, Polyhydroxystearic Acid, Polysorbate 20, Potassium Cetyl Phosphate, Propanediol, Rosmarinus Officinalis (Rosemary) Extract, Tocopherol, Xanthan Gum, Water (Aqua)

Questions?

1-888-676-3890